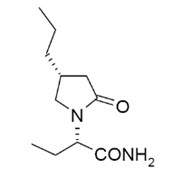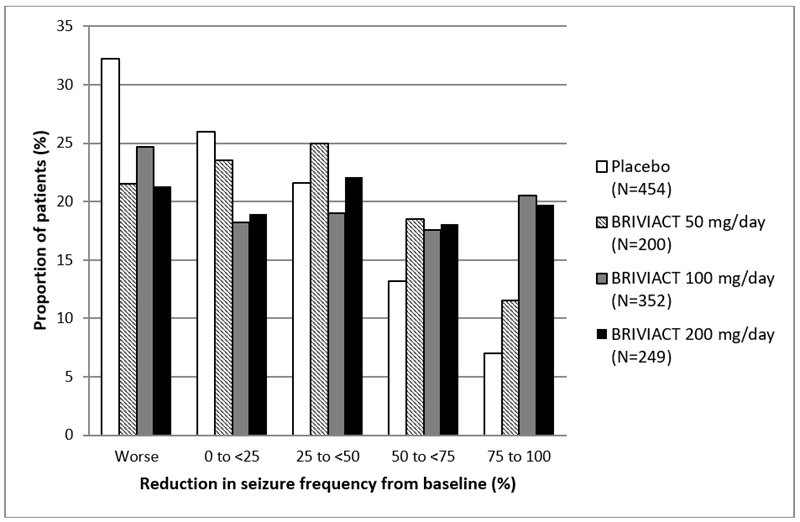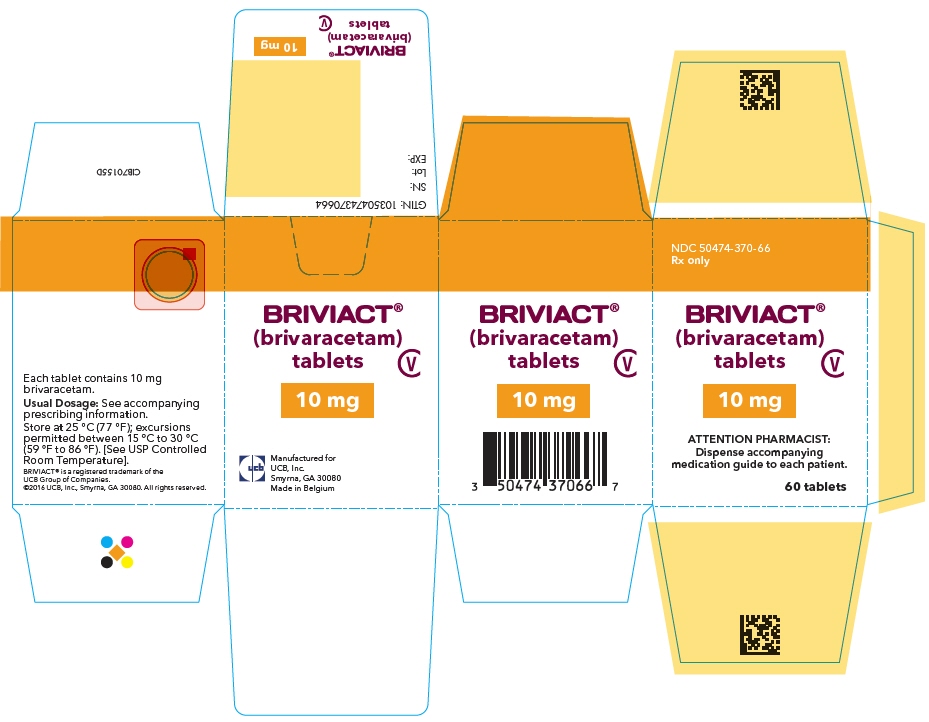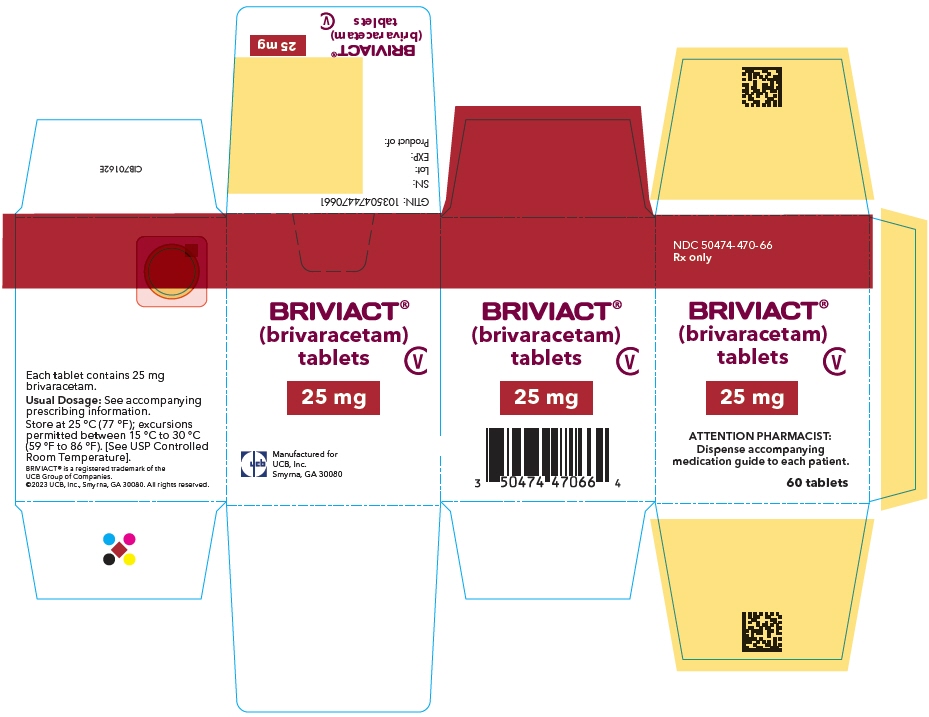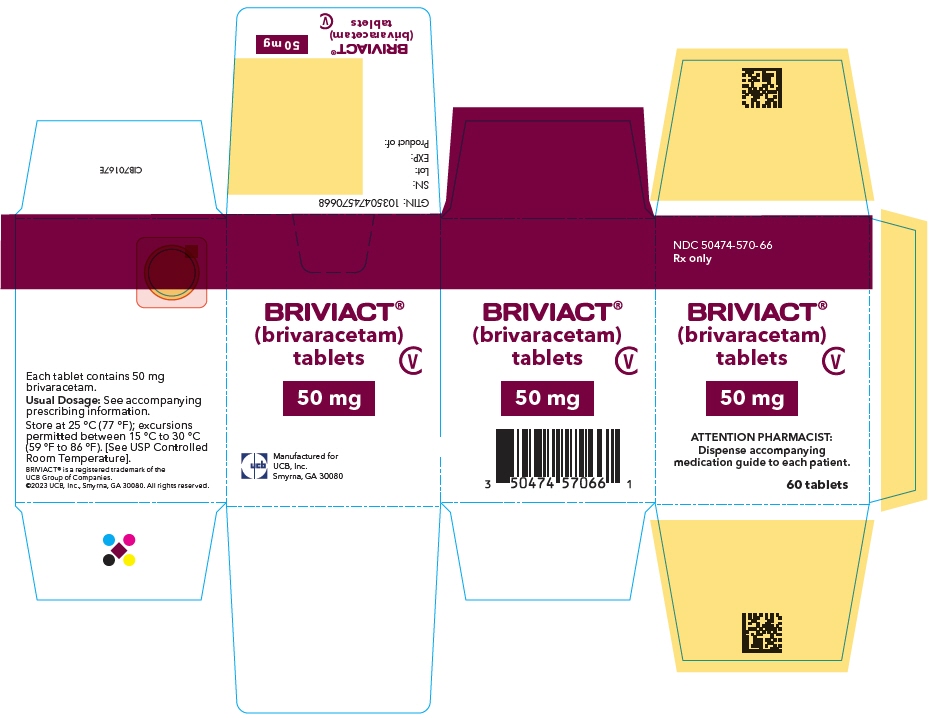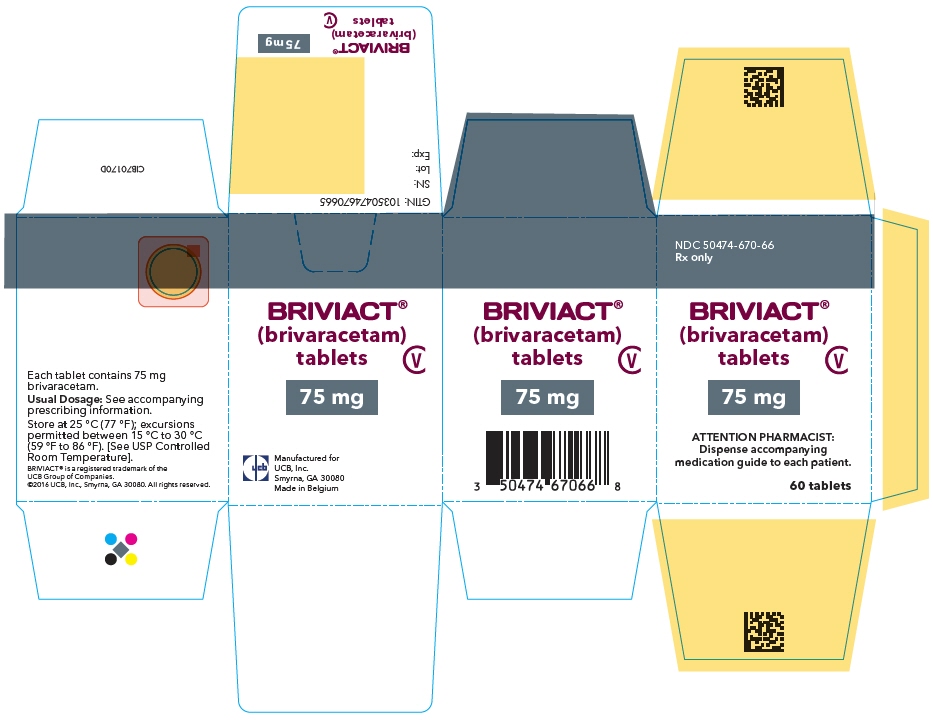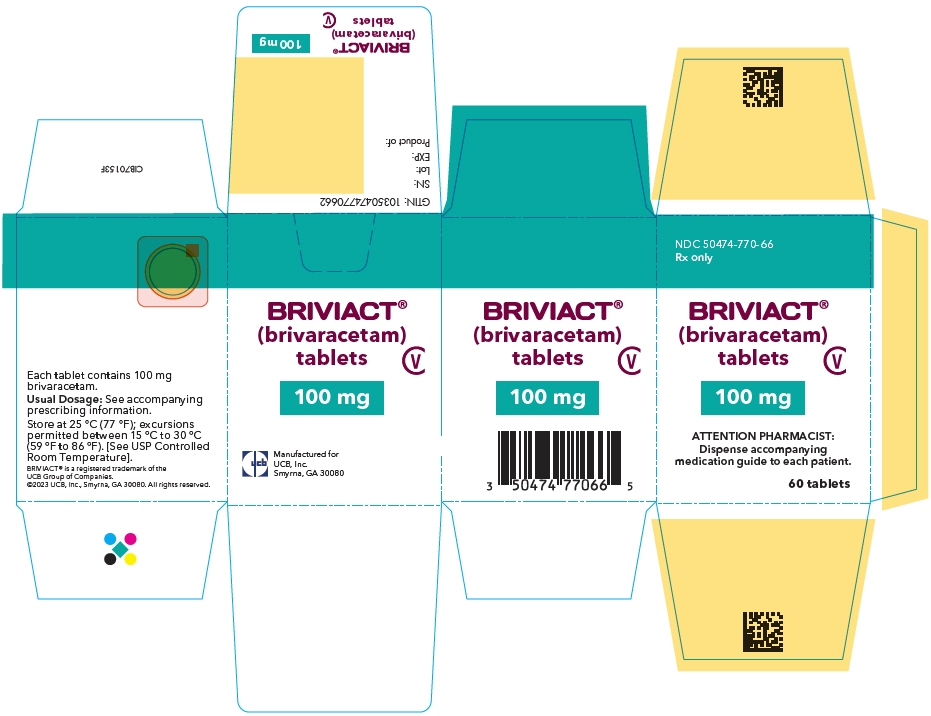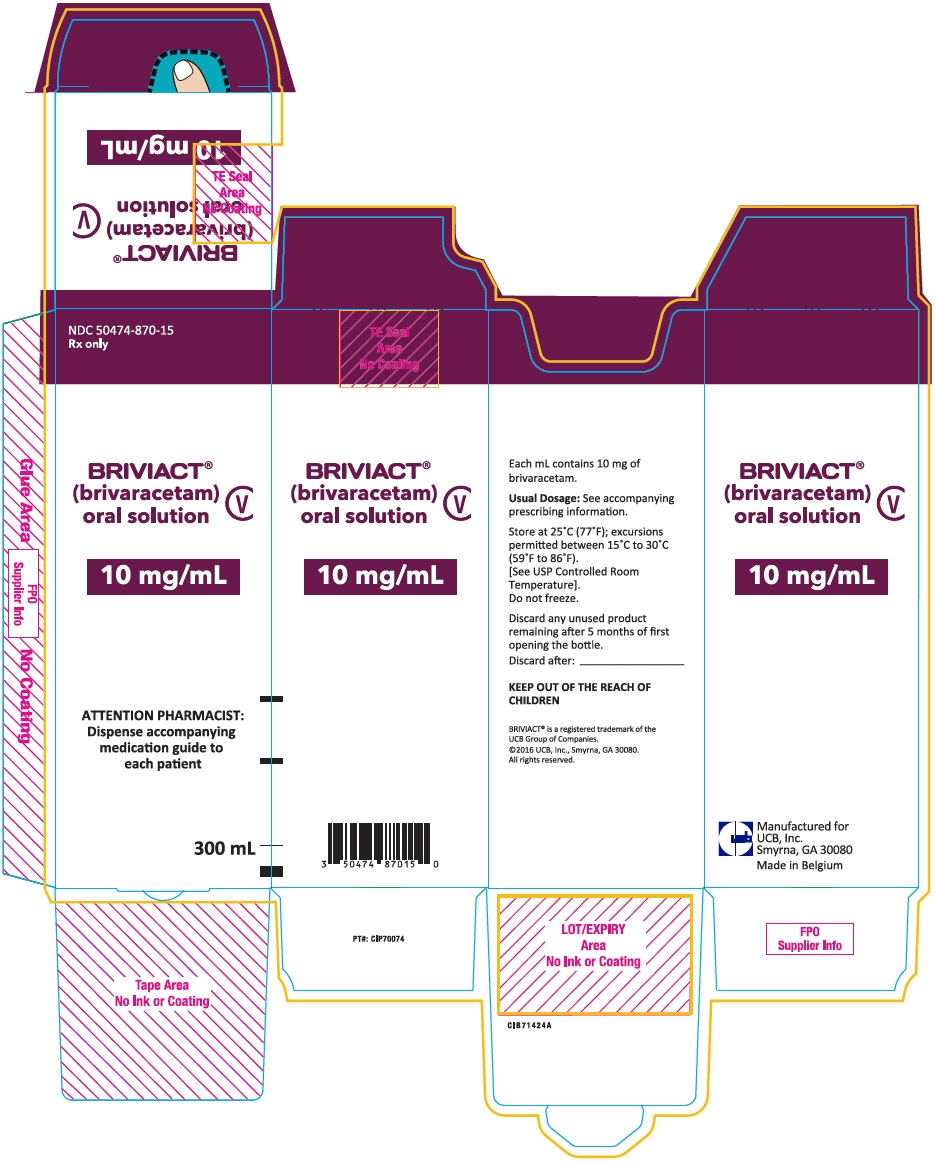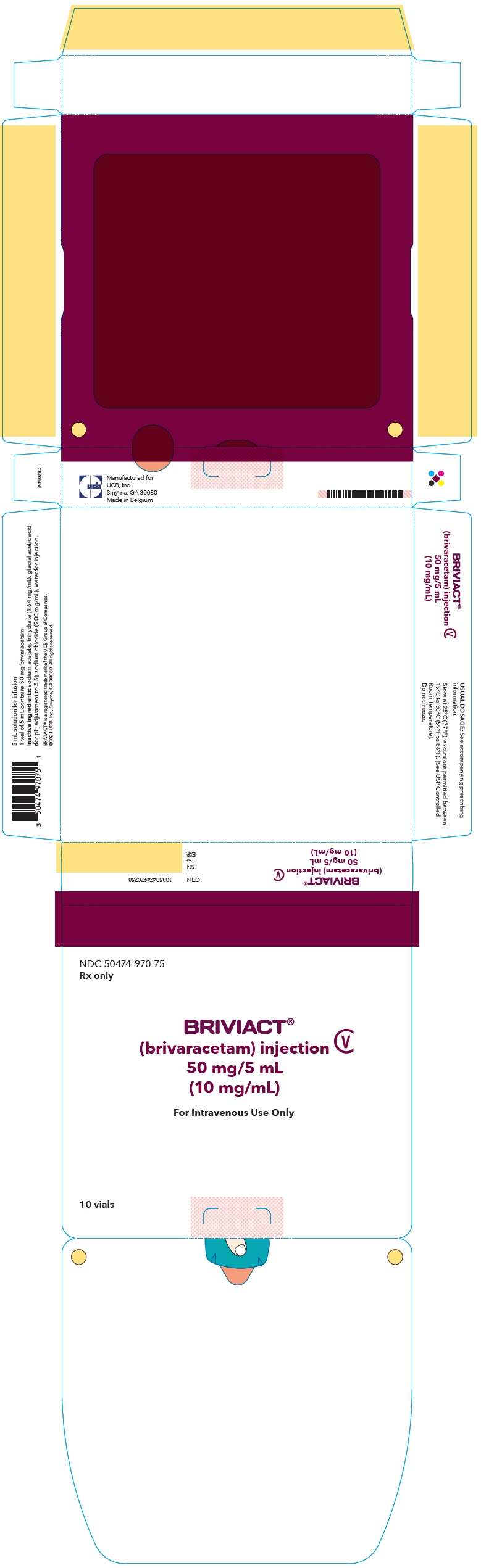 DRUG LABEL: Briviact
NDC: 50474-370 | Form: TABLET, FILM COATED
Manufacturer: UCB, Inc.
Category: prescription | Type: HUMAN PRESCRIPTION DRUG LABEL
Date: 20250910
DEA Schedule: CV

ACTIVE INGREDIENTS: BRIVARACETAM 10 mg/1 1
INACTIVE INGREDIENTS: CROSCARMELLOSE SODIUM; LACTOSE MONOHYDRATE; BETADEX; ANHYDROUS LACTOSE; MAGNESIUM STEARATE; POLYVINYL ALCOHOL, UNSPECIFIED; TALC; POLYETHYLENE GLYCOL 3350; TITANIUM DIOXIDE

HIGHLIGHTS OF PRESCRIBING INFORMATION

These highlights do not include all the information needed to use BRIVIACT®safely and effectively. See full prescribing information for BRIVIACT.
BRIVIACT®(brivaracetam) tablets, for oral use, CV
BRIVIACT®(brivaracetam) oral solution, CV
BRIVIACT®(brivaracetam) injection, for intravenous use, CV
Initial U.S. Approval: 2016

RECENT MAJOR CHANGES

Warnings and Precautions (5.5) | 8/2025

1 INDICATIONS AND USAGE

BRIVIACT is indicated for the treatment of partial-onset seizures in patients 1 month of age and older. (1)

2 DOSAGE AND ADMINISTRATION

- Adults (16 Years and Older):The recommended starting dosage for monotherapy or adjunctive therapy is 50 mg twice daily (100 mg per day). Based on individual patient tolerability and therapeutic response, the dosage may be adjusted down to 25 mg twice daily (50 mg per day) or up to 100 mg twice daily (200 mg per day). (2.1)
- Pediatric Patients (1 Month to less than 16 Years):The recommended dosage is based on body weight and is administered orally twice daily (2.1)
- Injection:for intravenous use only when oral administration is temporarily not feasible; dosing is the same as oral regimen. (2.1, 2.3)
- Hepatic Impairment:Dose adjustment is recommended for all stages of hepatic impairment. (2.5)

3 DOSAGE FORMS AND STRENGTHS

- Tablets: 10 mg, 25 mg, 50 mg, 75 mg, and 100 mg (3)
- Oral solution: 10 mg/mL (3)
- Injection: 50 mg/5 mL single-dose vial (3)

4 CONTRAINDICATIONS

Hypersensitivity to brivaracetam or any of the inactive ingredients in BRIVIACT. (4)

5 WARNINGS AND PRECAUTIONS

- Suicidal Behavior and Ideation: Monitor patients for suicidal behavior and ideation. (5.1)
- Neurological Adverse Reactions: Monitor for somnolence and fatigue, and advise patients not to drive or operate machinery until they have gained sufficient experience on BRIVIACT. (5.2)
- Psychiatric Adverse Reactions: Behavioral reactions including psychotic symptoms, irritability, depression, aggressive behavior, and anxiety; monitor patients for symptoms. (5.3)
- Hypersensitivity: Bronchospasm and Angioedema: Advise patients to seek immediate medical care. Discontinue and do not restart BRIVIACT if hypersensitivity occurs. (5.4)
- Serious Dermatologic Reactions: Discontinue BRIVIACT unless an alternative etiology is established (5.5)
- Withdrawal of Antiepileptic Drugs: BRIVIACT should be gradually withdrawn. (5.6)

6 ADVERSE REACTIONS

Adults:Most common adverse reactions (at least 5% for BRIVIACT and at least 2% more frequently than placebo) are somnolence/sedation, dizziness, fatigue, and nausea/vomiting. (6.1)

Pediatric Patients:Most common adverse reactions are similar to those seen in adult patients. (6.1)

To report SUSPECTED ADVERSE REACTIONS, contact UCB, Inc. at 1-844-599-2273 or FDA at 1-800-FDA-1088 orwww.fda.gov/medwatch.

7 DRUG INTERACTIONS

- Rifampin:Because of decreased concentrations, increasing BRIVIACT dosage in patients on concomitant rifampin is recommended. (2.6, 7.1)
- Carbamazepine:Because of increased exposure to carbamazepine metabolite, if tolerability issues arise, consider reducing carbamazepine dosage in patients on concomitant BRIVIACT. (7.2)
- Phenytoin:Because phenytoin concentrations can increase, phenytoin levels should be monitored in patients on concomitant BRIVIACT. (7.3)
- Levetiracetam:BRIVIACT had no added therapeutic benefit when co-administered with levetiracetam. (7.4)

8 USE IN SPECIFIC POPULATIONS

Pregnancy: Based on animal data, may cause fetal harm. (8.1)

FULL PRESCRIBING INFORMATION

1 INDICATIONS AND USAGE

BRIVIACT is indicated for the treatment of partial-onset seizures in patients 1 month of age and older.

2 DOSAGE AND ADMINISTRATION

2.1 Dosage Information

Monotherapy or Adjunctive Therapy

The recommended dosage for patients 1 month of age and older is included in Table 1. In pediatric patients weighing less than 50 kg, the recommended dosing regimen is dependent upon body weight. When initiating treatment, gradual dose escalation is not required. Dosage should be adjusted based on clinical response and tolerability.

Table 1: Recommended Dosage for Patients 1 Month of Age and Older
Age and Body Weight | Initial Dosage | Minimum and Maximum Maintenance Dosage
Adults (16 years and older) | 50 mg twice daily (100 mg per day) | 25 mg to 100 mg twice daily (50 mg to 200 mg per day)
Pediatric patients weighing 50 kg or more | 25 mg to 50 mg twice daily (50 mg to 100 mg per day) | 25 mg to 100 mg twice daily (50 mg to 200 mg per day)
Pediatric patients weighing 20 kg to less than 50 kg | 0.5 mg/kg to 1 mg/kg twice daily (1 mg/kg to 2 mg/kg per day) | 0.5 mg/kg to 2 mg/kg twice daily (1 mg/kg to 4 mg/kg per day)
Pediatric patients weighing 11 kg to less than 20 kg | 0.5 mg/kg to 1.25 mg/kg twice daily (1 mg/kg to 2.5 mg/kg per day) | 0.5 mg/kg to 2.5 mg/kg twice daily (1 mg/kg to 5 mg/kg per day)
Pediatric patients weighing less than 11 kg | 0.75 mg/kg to 1.5 mg/kg twice daily (1.5 mg/kg to 3 mg/kg per day) | 0.75 mg/kg to 3 mg/kg twice daily (1.5 mg/kg to 6 mg/kg per day)

BRIVIACT Injection Dosage

BRIVIACT injection may be used when oral administration is temporarily not feasible [see Dosage and Administration (2.3)]. BRIVIACT injection should be administered intravenously at the same dosage and same frequency as BRIVIACT tablets and oral solution.

The clinical study experience with BRIVIACT injection is up to 4 consecutive days of treatment.

2.2 Administration Instructions for BRIVIACT Tablets and BRIVIACT Oral Solution

BRIVIACT can be initiated with either intravenous or oral administration.

BRIVIACT tablets and oral solution may be taken with or without food.

BRIVIACT Tablets

BRIVIACT tablets should be swallowed whole with liquid. BRIVIACT tablets should not be chewed or crushed.

BRIVIACT Oral Solution

A calibrated measuring device is recommended to measure and deliver the prescribed dose accurately. A household teaspoon or tablespoon is not an adequate measuring device.

When using BRIVIACT oral solution, no dilution is necessary. BRIVIACT oral solution may also be administered using a nasogastric tube or gastrostomy tube.

Discard any unused BRIVIACT oral solution remaining after 5 months of first opening the bottle.

2.3 Preparation and Administration Instructions for BRIVIACT Injection

BRIVIACT injection is for intravenous use only.

Preparation

BRIVIACT injection can be administered intravenously without further dilution or may be mixed with diluents listed below.

Diluents

0.9% Sodium Chloride injection, USP
Lactated Ringer's injection
5% Dextrose injection, USP

Administration

BRIVIACT injection should be administered intravenously over 2 to 15 minutes.

Parenteral drug products should be inspected visually for particulate matter and discoloration prior to administration, whenever solution and container permit. Product with particulate matter or discoloration should not be used. BRIVIACT injection is for single dose only.

Storage and Stability

The diluted solution should not be stored for more than 4 hours at room temperature and may be stored in polyvinyl chloride (PVC) bags. Discard any unused portion of the BRIVIACT injection vial contents.

2.4 Discontinuation of BRIVIACT

Avoid abrupt withdrawal from BRIVIACT in order to minimize the risk of increased seizure frequency and status epilepticus [see Warnings and Precautions (5.6)and Clinical Studies (14)].

2.5 Patients with Hepatic Impairment

The recommended dosage for patients with hepatic impairment is included in Table 2 [see Use in Specific Populations (8.7)and Clinical Pharmacology (12.3)] .

Table 2: Recommended Dosage for Patients with Hepatic Impairment
Age and Body Weight | Initial Dosage | Maximum Maintenance Dosage
Adults (16 years and older) | 25 mg twice daily (50 mg per day) | 75 mg twice daily (150 mg per day)
Pediatric patients weighing 50 kg or more | 25 mg twice daily (50 mg per day) | 75 mg twice daily (150 mg per day)
Pediatric patients weighing 20 kg to less than 50 kg | 0.5 mg/kg twice daily (1 mg/kg per day) | 1.5 mg/kg twice daily (3 mg/kg per day)
Pediatric patients weighing 11 kg to less than 20 kg | 0.5 mg/kg twice daily (1 mg/kg per day) | 2 mg/kg twice daily (4 mg/kg per day)
Pediatric patients weighing less than 11 kg | 0.75 mg/kg twice daily (1.5 mg/kg per day) | 2.25 mg/kg twice daily (4.5 mg/kg per day)

2.6 Co-administration with Rifampin

Increase the BRIVIACT dosage in patients on concomitant rifampin by up to 100% (i.e., double the dosage) [see Drug Interactions (7.1)and Clinical Pharmacology (12.3)] .

3 DOSAGE FORMS AND STRENGTHS

Tablets

- 10 mg: white to off white, round, film-coated, and debossed with "u10" on one side.
- 25 mg: grey, oval, film-coated, and debossed with "u25" on one side.
- 50 mg: yellow, oval, film-coated, and debossed with "u50" on one side.
- 75 mg: purple, oval, film-coated, and debossed with "u75" on one side.
- 100 mg: green-grey, oval, film-coated, and debossed with "u100" on one side.

Oral Solution

- 10 mg/mL: slightly viscous, clear, colorless to yellowish, raspberry-flavored liquid.

Injection

- 50 mg in 5 mL in one single-dose vial. It is a clear, colorless, sterile solution .

4 CONTRAINDICATIONS

Hypersensitivity to brivaracetam or any of the inactive ingredients in BRIVIACT (bronchospasm and angioedema have occurred) [see Warnings and Precautions (5.4)] .

5 WARNINGS AND PRECAUTIONS

5.1 Suicidal Behavior and Ideation

Antiepileptic drugs (AEDs), including BRIVIACT, increase the risk of suicidal thoughts or behavior in patients taking these drugs for any indication. Patients treated with any AED for any indication should be monitored for the emergence or worsening of depression, suicidal thoughts or behavior, and/or any unusual changes in mood or behavior.

Pooled analyses of 199 placebo-controlled clinical trials (mono- and adjunctive therapy) of 11 different AEDs showed that patients randomized to one of the AEDs had approximately twice the risk (adjusted Relative Risk 1.8, 95% CI:1.2, 2.7) of suicidal thinking or behavior compared to patients randomized to placebo. In these trials, which had a median treatment duration of 12 weeks, the estimated incidence rate of suicidal behavior or ideation among 27,863 AED-treated patients was 0.43%, compared to 0.24% among 16,029 placebo-treated patients, representing an increase of approximately one case of suicidal thinking or behavior for every 530 patients treated. There were four suicides in drug-treated patients in the trials and none in placebo-treated patients, but the number is too small to allow any conclusion about drug effect on suicide.

The increased risk of suicidal thoughts or behavior with AEDs was observed as early as one week after starting drug treatment with AEDs and persisted for the duration of treatment assessed. Because most trials included in the analysis did not extend beyond 24 weeks, the risk of suicidal thoughts or behavior beyond 24 weeks could not be assessed.

The risk of suicidal thoughts or behavior was generally consistent among drugs in the data analyzed. The finding of increased risk with AEDs of varying mechanisms of action and across a range of indications suggests that the risk applies to all AEDs used for any indication. The risk did not vary substantially by age (5-100 years) in the clinical trials analyzed. Table 3 shows absolute and relative risk by indication for all evaluated AEDs.

Table 3: Risk of Suicidal Thoughts or Behaviors by Indication for Antiepileptic Drugs in the Pooled Analysis
Indication | Placebo Patients with Events Per 1000 Patients | Drug Patients with Events Per 1000 Patients | Relative Risk: Incidence of Events in Drug Patients/Incidence in Placebo Patients | Risk Difference: Additional Drug Patients with Events Per 1000 Patients
Epilepsy | 1.0 | 3.4 | 3.5 | 2.4
Psychiatric | 5.7 | 8.5 | 1.5 | 2.9
Other | 1.0 | 1.8 | 1.9 | 0.9
Total | 2.4 | 4.3 | 1.8 | 1.9

The relative risk for suicidal thoughts or behavior was higher in clinical trials in patients with epilepsy than in clinical trials in patients with psychiatric or other conditions, but the absolute risk differences were similar for the epilepsy and psychiatric indications.

Anyone considering prescribing BRIVIACT or any other AED must balance the risk of suicidal thoughts or behaviors with the risk of untreated illness. Epilepsy and many other illnesses for which AEDs are prescribed are themselves associated with morbidity and mortality and an increased risk of suicidal thoughts and behavior. Should suicidal thoughts and behavior emerge during treatment, consider whether the emergence of these symptoms in any given patient may be related to the illness being treated.

5.2 Neurological Adverse Reactions

BRIVIACT causes somnolence, fatigue, dizziness, and disturbance in coordination. Patients should be monitored for these signs and symptoms and advised not to drive or operate machinery until they have gained sufficient experience on BRIVIACT to gauge whether it adversely affects their ability to drive or operate machinery.

Somnolence and Fatigue

BRIVIACT causes dose-dependent increases in somnolence and fatigue-related adverse reactions (fatigue, asthenia, malaise, hypersomnia, sedation, and lethargy) [see Adverse Reactions (6.1)] . In the Phase 3 controlled adjunctive epilepsy trials, these events were reported in 25% of patients randomized to receive BRIVIACT at least 50 mg/day (20% at 50 mg/day, 26% at 100 mg/day, and 27% at 200 mg/day) compared to 14% of patients who received placebo. The risk is greatest early in treatment but can occur at any time.

Dizziness and Disturbance in Gait and Coordination

BRIVIACT causes adverse reactions related to dizziness and disturbance in gait and coordination (dizziness, vertigo, balance disorder, ataxia, nystagmus, gait disturbance, and abnormal coordination) [see Adverse Reactions (6.1)]. In the Phase 3 controlled adjunctive epilepsy trials, these events were reported in 16% of patients randomized to receive BRIVIACT at least 50 mg/day compared to 10% of patients who received placebo. The risk is greatest early in treatment but can occur at any time.

5.3 Psychiatric Adverse Reactions

BRIVIACT causes psychiatric adverse reactions. In the Phase 3 controlled adjunctive epilepsy trials, psychiatric adverse reactions were reported in approximately 13% of patients who received BRIVIACT (at least 50 mg/day) compared to 8% of patients who received placebo. Psychiatric events included both non-psychotic symptoms (irritability, anxiety, nervousness, aggression, belligerence, anger, agitation, restlessness, depression, depressed mood, tearfulness, apathy, altered mood, mood swings, affect lability, psychomotor hyperactivity, abnormal behavior, and adjustment disorder) and psychotic symptoms (psychotic disorder along with hallucination, paranoia, acute psychosis, and psychotic behavior). A total of 1.7% of adult patients treated with BRIVIACT discontinued treatment because of psychiatric reactions compared to 1.3% of patients who received placebo.

Psychiatric adverse reactions were also observed in open-label pediatric trials and were generally similar to those observed in adults [see Adverse Reactions (6.1)and Use in Specific Populations (8.4)].

5.4 Hypersensitivity: Bronchospasm and Angioedema

BRIVIACT can cause hypersensitivity reactions. Bronchospasm and angioedema have been reported in patients taking BRIVIACT. If a patient develops hypersensitivity reactions after treatment with BRIVIACT, the drug should be discontinued. BRIVIACT is contraindicated in patients with a prior hypersensitivity reaction to brivaracetam or any of the inactive ingredients [see Contraindications (4)] .

5.5 Serious Dermatologic Reactions

Serious dermatologic reactions, including Stevens-Johnson syndrome (SJS) and toxic epidermal necrolysis (TEN), have been reported in patients treated with BRIVIACT. Time to onset of the serious dermatologic reaction ranged from 3 to 45 days after BRIVIACT initiation in reported cases. BRIVIACT should be discontinued at the first sign of a rash, unless the rash is clearly not drug-related. If signs or symptoms suggest a serious dermatologic reaction, use of BRIVIACT should not be resumed and alternative therapy should be considered.

5.6 Withdrawal of Antiepileptic Drugs

As with most antiepileptic drugs, BRIVIACT should generally be withdrawn gradually because of the risk of increased seizure frequency and status epilepticus [see Dosage and Administration (2.4)and Clinical Studies (14)] . But if withdrawal is needed because of a serious adverse event, rapid discontinuation can be considered.

6 ADVERSE REACTIONS

The following serious adverse reactions are described elsewhere in labeling:

- Suicidal Behavior and Ideation [see Warnings and Precautions (5.1)]
- Neurological Adverse Reactions [see Warnings and Precautions (5.2)]
- Psychiatric Adverse Reactions [see Warnings and Precautions (5.3)]
- Hypersensitivity: Bronchospasm and Angioedema [see Warnings and Precautions (5.4)]
- Serious Dermatologic Reactions [see Warnings and Precautions (5.5)]
- Withdrawal of Antiepileptic Drugs [see Warnings and Precautions (5.6)]

6.1 Clinical Trials Experience

Because clinical trials are conducted under widely varying conditions, adverse reaction rates observed in the clinical trials of a drug cannot be directly compared to rates in the clinical trials of another drug and may not reflect the rates observed in practice.

In all controlled and uncontrolled trials performed in adult epilepsy patients, BRIVIACT was administered as adjunctive therapy to 2437 patients. Of these patients, 1929 were treated for at least 6 months, 1500 for at least 12 months, 1056 for at least 24 months, and 758 for at least 36 months. A total of 1558 patients (1099 patients treated with BRIVIACT and 459 patients treated with placebo) constituted the safety population in the pooled analysis of Phase 3 placebo-controlled studies in patients with partial-onset seizures (Studies 1, 2, and 3) [see Clinical Studies (14)] . The adverse reactions presented in Table 4 are based on this safety population; the median length of treatment in these studies was 12 weeks. Of the patients in those studies, approximately 51% were male, 74% were Caucasian, and the mean age was 38 years.

In the Phase 3 controlled epilepsy studies, adverse events occurred in 68% of patients treated with BRIVIACT and 62% treated with placebo. The most common adverse reactions occurring at a frequency of at least 5% in patients treated with BRIVIACT doses of at least 50 mg/day and greater than placebo were somnolence and sedation (16%), dizziness (12%), fatigue (9%), and nausea and vomiting symptoms (5%).

The discontinuation rates due to adverse events were 5%, 8%, and 7% for patients randomized to receive BRIVIACT at the recommended doses of 50 mg, 100 mg, and 200 mg/day, respectively, compared to 4% in patients randomized to receive placebo.

Table 4 lists adverse reactions for BRIVIACT that occurred at least 2% more frequently for BRIVIACT doses of at least 50 mg/day than placebo.

Table 4: Adverse Reactions in Pooled Placebo-Controlled Adjunctive Therapy Studies in Adult Patients with Partial-Onset Seizures (BRIVIACT 50 mg/day, 100 mg/day, and 200 mg/day)
Adverse Reactions | BRIVIACT (N=803) % | Placebo (N=459) %
Gastrointestinal disorders
Nausea/vomiting symptoms | 5 | 3
Constipation | 2 | 0
Nervous system disorders
Somnolence and sedation | 16 | 8
Dizziness | 12 | 7
Fatigue | 9 | 4
Cerebellar coordination and balance disturbances [Cerebellar coordination and balance disturbances includes ataxia, balance disorder, coordination abnormal, and nystagmus.] | 3 | 1
Psychiatric disorders
Irritability | 3 | 1

There was no apparent dose-dependent increase in adverse reactions listed in Table 4 with the exception of somnolence and sedation.

Pediatric Patients

Safety of BRIVIACT was evaluated in two open-label, safety and pharmacokinetic trials in pediatric patients 2 months to less than 16 years of age. Across studies of pediatric patients with partial onset seizures, 186 patients received BRIVIACT oral solution or tablet, of whom 123 received BRIVIACT for at least 12 months. Adverse reactions reported in clinical studies of pediatric patients were generally similar to those seen in adult patients. Decreased appetite was also observed in these pediatric trials.

Hematologic Abnormalities

BRIVIACT can cause hematologic abnormalities. In the Phase 3 controlled adjunctive epilepsy studies, a total of 1.8% of BRIVIACT-treated patients and 1.1% of placebo-treated patients had at least one clinically significant decreased white blood cell count (<3.0 × 10^9/L), and 0.3% of BRIVIACT-treated patients and 0% of placebo-treated patients had at least one clinically significant decreased neutrophil count (<1.0 × 10^9/L).

Adverse Reactions with BRIVIACT Injection

Adverse reactions with BRIVIACT injection administered to adults and pediatric patients 2 months to 16 years of age were generally similar to those observed with BRIVIACT tablets. Other adverse events that occurred in at least 3% of adult patients who received BRIVIACT injection included dysgeusia, euphoric mood, feeling drunk, and infusion site pain.

Comparison by Sex

There were no significant differences by sex in the incidence of adverse reactions.

6.2 Postmarketing Experience

The following adverse reactions have been identified during post approval use of BRIVIACT. Because these reactions are reported voluntarily from a population of uncertain size, it is not always possible to reliably estimate their frequency or establish a causal relationship to drug exposure.

Skin and Subcutaneous Tissue Disorders:Serious dermatologic reactions (e.g., Stevens-Johnson syndrome and toxic epidermal necrolysis) [see Warnings and Precautions (5.5)]

7 DRUG INTERACTIONS

7.1 Rifampin

Co-administration with rifampin decreases BRIVIACT plasma concentrations likely because of CYP2C19 induction [see Clinical Pharmacology (12.3)] . Prescribers should increase the BRIVIACT dose by up to 100% (i.e., double the dosage) in patients while receiving concomitant treatment with rifampin [see Dosage and Administration (2.6)] .

7.2 Carbamazepine

Co-administration with carbamazepine may increase exposure to carbamazepine-epoxide, the active metabolite of carbamazepine. Though available data did not reveal any safety concerns, if tolerability issues arise when co-administered, carbamazepine dose reduction should be considered [see Clinical Pharmacology (12.3)] .

7.3 Phenytoin

Because BRIVIACT can increase plasma concentrations of phenytoin, phenytoin levels should be monitored in patients when concomitant BRIVIACT is added to or discontinued from ongoing phenytoin therapy [see Clinical Pharmacology (12.3)] .

7.4 Levetiracetam

BRIVIACT provided no added therapeutic benefit to levetiracetam when the two drugs were co-administered [see Clinical Studies (14)].

8 USE IN SPECIFIC POPULATIONS

8.1 Pregnancy

Pregnancy Exposure Registry

There is a pregnancy exposure registry that monitors pregnancy outcomes in women exposed to antiepileptic drugs (AEDs), such as BRIVIACT, during pregnancy. Encourage patients who are taking BRIVIACT during pregnancy to enroll in the North American Antiepileptic Drug (NAAED) Pregnancy Registry by calling the toll free number 1-888-233-2334 or visiting http://www.aedpregnancyregistry.org/.

Risk Summary

Available data from the North American Antiepileptic Drug (NAAED) pregnancy registry, a prospective cohort study, case reports, and a case series are insufficient to identify a risk of major birth defects, miscarriage or other maternal or fetal outcomes associated with BRIVIACT use during pregnancy. In animal studies, brivaracetam produced evidence of developmental toxicity (increased embryofetal mortality and decreased fetal body weights in rabbits; decreased growth, delayed sexual maturation, and long-term neurobehavioral changes in rat offspring) at maternal plasma exposures greater than clinical exposures [see Data] .

The background risk of major birth defects and miscarriage for the indicated population is unknown. All pregnancies have a background risk of birth defect, loss, or other adverse outcomes. In the U.S. general population, the estimated background risk of major birth defects and miscarriage in clinically recognized pregnancies is 2-4% and 15-20%, respectively.

Data

Animal Data

Oral administration of brivaracetam (0, 150, 300, or 600 mg/kg/day) to pregnant rats during the period of organogenesis did not produce any significant maternal or embryofetal toxicity. The highest dose tested was associated with maternal plasma exposures (AUC) approximately 30 times exposures in humans at the maximum recommended dose (MRD) of 200 mg/day.

Oral administration of brivaracetam (0, 30, 60, 120, or 240 mg/kg/day) to pregnant rabbits during the period of organogenesis resulted in embryofetal mortality and decreased fetal body weights at the highest dose tested, which was also maternally toxic. The highest no-effect dose (120 mg/kg/day) was associated with maternal plasma exposures approximately 4 times human exposures at the MRD.

When brivaracetam (0, 150, 300, or 600 mg/kg/day) was orally administered to rats throughout pregnancy and lactation, decreased growth, delayed sexual maturation (female), and long-term neurobehavioral changes were observed in the offspring at the highest dose. The highest no-effect dose (300 mg/kg/day) was associated with maternal plasma exposures approximately 7 times human exposures at the MRD.

Brivaracetam was shown to readily cross the placenta in pregnant rats after a single oral (5 mg/kg) dose of^14C-brivaracetam. From 1 hour post dose, radioactivity levels in fetuses, amniotic fluid, and placenta were similar to those measured in maternal blood.

8.2 Lactation

Risk Summary

Data from published literature indicate that brivaracetam is present in human milk. There is insufficient information on the effects of brivaracetam on the breastfed infant or on milk production.

The developmental and health benefits of breastfeeding should be considered along with the mother's clinical need for BRIVIACT and any potential adverse effects on the breastfed infant from BRIVIACT or from the underlying maternal condition.

8.4 Pediatric Use

Safety and effectiveness of BRIVIACT have been established in pediatric patients 1 month to less than 16 years of age. Use of BRIVIACT in these age groups is supported by evidence from adequate and well-controlled studies of BRIVIACT in adults with partial-onset seizures, pharmacokinetic data from adult and pediatric patients, and safety data in pediatric patients 2 months to less than 16 years of age [see Dosage and Administration (2.1), Warnings and Precautions (5.3), Adverse Reactions (6.1), Clinical Pharmacology (12.3), and Clinical Studies (14)] .

Safety and effectiveness in pediatric patients below the age of 1 month have not been established.

Juvenile Animal Toxicity Data

The potential adverse effects of brivaracetam on postnatal growth and development were investigated in juvenile rats and dogs. Oral administration (0, 150, 300, or 600 mg/kg/day) to rats during the neonatal and juvenile periods of development (approximately equivalent to neonatal through adolescent development in humans) resulted in increased mortality, decreased body weight gain, delayed male sexual maturation, and adverse neurobehavioral effects at the highest dose tested and decreased brain size and weight at all doses. Therefore, a no-effect dose was not established; the lowest dose tested in juvenile rats was associated with plasma exposures (AUC) approximately 2 times those in children and adolescents at the recommended maintenance dose. In dogs, oral administration (0, 15, 30, or 100 mg/kg/day) throughout the neonatal and juvenile periods of development induced liver changes similar to those observed in adult animals at the highest dose but produced no adverse effects on growth, bone density or strength, neurological testing, or neuropathology evaluation. The overall no-effect dose (30 mg/kg/day) and the no-effect dose for adverse effects on developmental parameters (100 mg/kg/day) were associated with plasma exposures approximately equal to and 4 times, respectively, those in children and adolescents at the recommended maintenance dose.

8.5 Geriatric Use

There were insufficient numbers of patients 65 years of age and older in the double-blind, placebo-controlled epilepsy trials (n=38) to allow adequate assessment of the effectiveness of BRIVIACT in this population. In general, dose selection for an elderly patient should be judicious, usually starting at the low end of the dosing range, reflecting the greater frequency of decreased hepatic, renal, or cardiac function, and of concomitant disease or other drug therapy [see Clinical Pharmacology (12.3)] .

8.6 Renal Impairment

Dose adjustments are not required for patients with impaired renal function. There are no data in patients with end-stage renal disease undergoing dialysis, and use of BRIVIACT is not recommended in this patient population [see Clinical Pharmacology (12.3)] .

8.7 Hepatic Impairment

Because of increases in BRIVIACT exposure, dosage adjustment is recommended for all stages of hepatic impairment [see Dosage and Administration (2.5)and Clinical Pharmacology (12.3)] .

9 DRUG ABUSE AND DEPENDENCE

9.1 Controlled Substance

BRIVIACT contains brivaracetam and is listed as a Schedule V controlled substance.

9.2 Abuse

In a human abuse potential study, single doses of BRIVIACT at therapeutic and supratherapeutic doses were compared to alprazolam (C-IV) (1.5 mg and 3 mg). BRIVIACT at the recommended single dose (50 mg) caused fewer sedative and euphoric effects than alprazolam; however, BRIVIACT at supratherapeutic single doses (200 mg and 1000 mg) was similar to alprazolam on other measures of abuse.

9.3 Dependence

There was no evidence of physical dependence potential or a withdrawal syndrome with BRIVIACT in a pooled review of placebo-controlled adjunctive therapy studies [see Warnings and Precautions (5.6)].

10 OVERDOSAGE

There is limited clinical experience with BRIVIACT overdose in humans. Somnolence and dizziness were reported in a patient taking a single dose of 1400 mg (14 times the highest recommended single dose) of BRIVIACT. The following adverse reactions were reported with BRIVIACT overdose: vertigo, balance disorder, fatigue, nausea, diplopia, anxiety, and bradycardia. In general, the adverse reactions associated with BRIVIACT overdose were consistent with the known adverse reactions.

There is no specific antidote for overdose with BRIVIACT. In the event of overdose, standard medical practice for the management of any overdose should be used. An adequate airway, oxygenation, and ventilation should be ensured; monitoring of cardiac rate and rhythm and vital signs is recommended. A certified poison control center should be contacted for updated information on the management of overdose with BRIVIACT. There are no data on the removal of brivaracetam using hemodialysis, but because less than 10% of brivaracetam is excreted in urine, hemodialysis is not expected to enhance BRIVIACT clearance.

11 DESCRIPTION

The chemical name of BRIVIACT (brivaracetam) is (2S)-2-[(4R)-2-oxo-4-propyltetrahydro-1 H-pyrrol-1-yl] butanamide. Its molecular formula is C11H20N2O2and its molecular weight is 212.29. The chemical structure is:

Brivaracetam is a white to off-white crystalline powder. It is very soluble in water, buffer (pH 1.2, 4.5, and 7.4), ethanol, methanol, and glacial acetic acid. It is freely soluble in acetonitrile and acetone and soluble in toluene. It is very slightly soluble in n-hexane.

Tablets

BRIVIACT tablets are for oral administration and contain the following inactive ingredients: croscarmellose sodium, lactose monohydrate, betadex (β-cyclodextrin), anhydrous lactose, magnesium stearate, and film coating agents specified below:

10 mg tablets: polyvinyl alcohol, talc, polyethylene glycol 3350, titanium dioxide
25 mg and 100 mg tablets: polyvinyl alcohol, talc, polyethylene glycol 3350, titanium dioxide, yellow iron oxide, black iron oxide
50 mg tablets: polyvinyl alcohol, talc, polyethylene glycol 3350, titanium dioxide, yellow iron oxide, red iron oxide
75 mg tablets: polyvinyl alcohol, talc, polyethylene glycol 3350, titanium dioxide, yellow iron oxide, red iron oxide, black iron oxide

Oral Solution

BRIVIACT oral solution contains 10 mg of brivaracetam per mL. The inactive ingredients are sodium citrate, anhydrous citric acid, methylparaben, sodium carboxymethylcellulose, sucralose, sorbitol solution, glycerin, raspberry flavor, and purified water.

Injection

BRIVIACT injection is a clear, colorless liquid provided as a sterile, preservative-free solution. BRIVIACT injection contains 10 mg brivaracetam per mL for intravenous administration. One vial contains 50 mg of brivaracetam drug substance. It contains the following inactive ingredients: sodium acetate, trihydrate (1.64 mg/mL), glacial acetic acid (for pH adjustment to 5.5), sodium chloride (9.00 mg/mL), and water for injection.

12 CLINICAL PHARMACOLOGY

12.1 Mechanism of Action

The precise mechanism by which BRIVIACT exerts its anticonvulsant activity is not known. Brivaracetam displays a high and selective affinity for synaptic vesicle protein 2A (SV2A) in the brain, which may contribute to the anticonvulsant effect.

12.2 Pharmacodynamics

Interactions with Alcohol

In a pharmacokinetic and pharmacodynamic interaction study in healthy subjects, co-administration of BRIVIACT (single dose 200 mg [2 times greater than the highest recommended single dose]) and ethanol (continuous intravenous infusion to achieve a blood alcohol concentration of 60 mg/100 mL during 5 hours) increased the effects of alcohol on psychomotor function, attention, and memory. Co-administration of BRIVIACT and ethanol caused a larger decrease from baseline in saccadic peak velocity, smooth pursuit, adaptive tracking performance, and Visual Analog Scale (VAS) alertness, and a larger increase from baseline in body sway and in saccadic reaction time compared with BRIVIACT alone or ethanol alone. The immediate word recall scores were generally lower for BRIVIACT when co-administered with ethanol.

Cardiac Electrophysiology

At a dose 4 times the maximum recommended dose, BRIVIACT did not prolong the QT interval to a clinically relevant extent.

12.3 Pharmacokinetics

BRIVIACT tablets, oral solution, and injection can be used interchangeably. Brivaracetam exhibits linear and time-independent pharmacokinetics at the approved doses.

The pharmacokinetics of brivaracetam are similar when used as monotherapy or as adjunctive therapy for the treatment of partial-onset seizures.

Absorption

Brivaracetam is highly permeable and is rapidly and almost completely absorbed after oral administration. Pharmacokinetics is dose-proportional from 10 to 600 mg (a range that extends beyond the minimum and maximum single-administration dose levels described in Dosage and Administration [see Dosage and Administration (2.1)]). The median Tmaxfor tablets taken without food is 1 hour (range 0.25 to 3 hours). Co-administration with a high-fat meal slowed absorption, but the extent of absorption remained unchanged. Specifically, when a 50 mg tablet was administered with a high-fat meal, Cmax(maximum brivaracetam plasma concentration during a dose interval, an exposure metric) was decreased by 37% and Tmaxwas delayed by 3 hours, but AUC (area under the brivaracetam plasma concentration versus time curve, an exposure metric) was essentially unchanged (decreased by 5%).

Distribution

Brivaracetam is weakly bound to plasma proteins (≤20%). The volume of distribution is 0.5 L/kg, a value close to that of the total body water. Brivaracetam is rapidly and evenly distributed in most tissues.

Elimination

Metabolism

Brivaracetam is primarily metabolized by hydrolysis of the amide moiety to form the corresponding carboxylic acid metabolite, and secondarily by hydroxylation on the propyl side chain to form the hydroxy metabolite. The hydrolysis reaction is mediated by hepatic and extra-hepatic amidase. The hydroxylation pathway is mediated primarily by CYP2C19. In human subjects possessing genetic variations in CYP2C19, production of the hydroxy metabolite is decreased 2-fold or 10-fold, while the blood level of brivaracetam itself is increased by 22% or 42%, respectively, in individuals with one or both mutated alleles. CYP2C19 poor metabolizers and patients using inhibitors of CYP2C19 may require dose reduction. An additional hydroxy acid metabolite is created by hydrolysis of the amide moiety on the hydroxy metabolite or hydroxylation of the propyl side chain on the carboxylic acid metabolite (mainly by CYP2C9). None of the 3 metabolites are pharmacologically active.

Excretion

Brivaracetam is eliminated primarily by metabolism and by excretion in the urine. More than 95% of the dose, including metabolites, is excreted in the urine within 72 hours after intake. Fecal excretion accounts for less than 1% of the dose. Less than 10% of the dose is excreted unchanged in the urine. Thirty-four percent of the dose is excreted as the carboxylic acid metabolite in urine. The terminal plasma half-life (t1/2) is approximately 9 hours.

Specific Populations

Age

Pediatric Patients (2 months to less than 16 years): An open-label, single-arm, multicenter, pharmacokinetic study with a 3-week evaluation period and fixed 3-step up-titration using BRIVIACT oral solution was conducted in 99 pediatric patients 2 months to less than 16 years of age. In those patients, plasma concentrations were shown to be dose-proportional. The pediatric pharmacokinetic profile for BRIVIACT was determined in a population pharmacokinetic analysis using sparse plasma concentration data obtained in three open-label studies in 255 adult and pediatric patients with epilepsy 2 months to 22 years of age that received intravenous, oral solution, or oral tablet formulations.

A weight-based dosing regimen is necessary to achieve brivaracetam exposures in pediatric patients 1 month to less than 16 years of age that are similar to those observed in adults treated at effective doses of BRIVIACT [ see Dosage and Administration (2.2)]. The estimated plasma clearance was 1.09 L/h, 1.81 L/h, and 3.11 L/h for pediatric patients weighing 11 kg, 20 kg, and 50 kg, respectively. In comparison, plasma clearance was estimated at 3.58 L/h in adult patients (70 kg body weight).

Geriatric Population: In a study in elderly subjects (65 to 79 years old; creatinine clearance 53 to 98 mL/min/1.73 m^2) receiving BRIVIACT 200 mg twice daily (2 times the highest recommended dosage), the plasma half-life of brivaracetam was 7.9 hours and 9.3 hours in the 65 to 75 and >75 years groups, respectively. The steady-state plasma clearance of brivaracetam was slightly lower (0.76 mL/min/kg) than in young healthy controls (0.83 mL/min/kg).

Sex

There were no differences observed in the pharmacokinetics of brivaracetam between male and female subjects.

Race/Ethnicity

A population pharmacokinetic analysis comparing Caucasian and non-Caucasian patients showed no significant pharmacokinetic difference.

Renal Impairment

A study in adult subjects with severe renal impairment (creatinine clearance <30 mL/min/1.73m^2and not requiring dialysis) revealed that the plasma AUC of brivaracetam was moderately increased (21%) relative to healthy controls, while the AUCs of the acid, hydroxy, and hydroxyacid metabolites were increased 3-fold, 4-fold, and 21-fold, respectively. The renal clearance of these inactive metabolites was decreased 10-fold. Brivaracetam has not been studied in patients undergoing hemodialysis [see Use in Specific Populations (8.6)].

Hepatic Impairment

A pharmacokinetic study in adult subjects with hepatic cirrhosis, Child-Pugh grades A, B, and C, showed 50%, 57%, and 59% increases in brivaracetam exposure, respectively, compared to matched healthy controls. The effect of hepatic impairment on brivaracetam pharmacokinetics in pediatric patients is expected to be comparable to the effect observed in adults [see Dosage and Administration (2.5)and Use in Specific Populations (8.7)].

Drug Interaction Studies

In Vitro Assessment of Drug Interactions

Drug-Metabolizing Enzyme Inhibition

Brivaracetam did not inhibit CYP1A2, 2A6, 2B6, 2C8, 2C9, 2D6, or 3A4. Brivaracetam weakly inhibited CYP2C19 and would not be expected to cause significant inhibition of CYP2C19 in humans. Brivaracetam was an inhibitor of epoxide hydrolase, (IC50= 8.2 μM), suggesting that brivaracetam can inhibit the enzyme in vivo.

Drug-Metabolizing Enzyme Induction

Brivaracetam at concentrations up to 10 μM caused little or no change of mRNA expression of CYP1A2, 2B6, 2C9, 2C19, 3A4, and epoxide hydrolase. It is unlikely that brivaracetam will induce these enzymes in vivo.

Transporters

Brivaracetam was not a substrate of P-gp, MRP1, or MRP2. Brivaracetam did not inhibit or weakly inhibit BCRP, BSEP, MATE1, MATE2/K, MRP2, OAT1, OAT3, OCT1, OCT2, OATP1B1, OATP1B3, or P-gp, suggesting that brivaracetam is unlikely to inhibit these transporters in vivo.

In Vivo Assessment of Drug Interactions

Drug Interaction Studies with Antiepileptic Drugs (AEDs)

Potential interactions between BRIVIACT (25 mg twice daily to 100 mg twice daily) and other AEDs were investigated in a pooled analysis of plasma drug concentrations from all Phase 2 and 3 studies and in a population exposure-response analysis of placebo-controlled, Phase 3 studies in adjunctive therapy in the treatment of partial-onset seizures. None of the interactions require changes in the dose of BRIVIACT. Interactions with carbamazepine and phenytoin can be clinically important [see Drug Interactions (7.2)and (7.3)] . The interactions are summarized in Table 5.

Table 5: Drug Interactions Between BRIVIACT and Concomitant Antiepileptic Drugs
Concomitant AED | Influence of AED on BRIVIACT | Influence of BRIVIACT on AED
Carbamazepine | 26% decrease in plasma concentration | None for carbamazepine
 |  | Increase of carbamazepine-epoxide metabolite [Brivaracetam is a reversible inhibitor of epoxide hydrolase resulting in an increased concentration of carbamazepine epoxide, an active metabolite of carbamazepine. The carbamazepine epoxide plasma concentration increased up to 198% at a BRIVIACT dose of 100 mg twice daily.] [see Drug Interactions (7.2)]
Lacosamide | No data | None
Lamotrigine | None | None
Levetiracetam | None | None
Oxcarbazepine | None | None on the active monohydroxy metabolite derivative (MHD)
Phenobarbital | 19% decrease in plasma concentration | None
Phenytoin | 21% decrease in plasma concentration | Up to 20% increase in plasma concentration [see Drug Interactions (7.3)] [At a supratherapeutic dose of 400 mg/day brivaracetam, there was a 20% increase in phenytoin plasma concentration.]
Pregabalin | No data | None
Topiramate | None | None
Valproic acid | None | None
Zonisamide | No data | None

Drug Interaction Studies with Other Drugs

Effect of Other Drugs on BRIVIACT

Co-administration with CYP inhibitors or transporter inhibitors is unlikely to significantly affect brivaracetam exposure.

Co-administration with rifampin decreases brivaracetam plasma concentrations by 45%, an effect that is probably the result of CYP2C19 induction [see Dosage and Administration (2.6)and Drug Interactions (7.1)].

Oral Contraceptives

Co-administration of BRIVIACT 200 mg twice daily (twice the recommended maximum daily dosage) with an oral contraceptive containing ethinylestradiol (0.03 mg) and levonorgestrel (0.15 mg) reduced estrogen and progestin AUCs by 27% and 23%, respectively, without impact on suppression of ovulation. However, co-administration of BRIVIACT 50 mg twice daily with an oral contraceptive containing ethinylestradiol (0.03 mg) and levonorgestrel (0.15 mg) did not significantly influence the pharmacokinetics of either substance. The interaction is not expected to be of clinical significance.

13 NONCLINICAL TOXICOLOGY

13.1 Carcinogenesis, Mutagenesis, Impairment of Fertility

Carcinogenesis

In a carcinogenicity study in mice, oral administration of brivaracetam (0, 400, 550, or 700 mg/kg/day) for 104 weeks increased the incidence of liver tumors (hepatocellular adenoma and carcinoma) in male mice at the two highest doses tested. At the dose (400 mg/kg) not associated with an increase in liver tumors, plasma exposures (AUC) were approximately equal to those in humans at the maximum recommended dose (MRD) of 200 mg/day. Oral administration (0, 150, 230, 450, or 700 mg/kg/day) to rats for 104 weeks resulted in an increased incidence of thymus tumors (benign thymoma) in female rats at the highest dose tested. At the highest dose not associated with an increase in thymus tumors, plasma exposures were approximately 9 times those in humans at the MRD.

Mutagenesis

Brivaracetam was negative for genotoxicity in in vitro(Ames, mouse lymphoma, and CHO chromosomal aberration) and in vivo(rat bone marrow micronucleus) assays.

Impairment of Fertility

Oral administration of brivaracetam (0, 100, 200, or 400 mg/kg/day) to male and female rats prior to and throughout mating and early gestation produced no adverse effects on fertility. The highest dose tested was associated with plasma exposures approximately 6 (males) and 13 (females) times those in humans at the MRD.

14 CLINICAL STUDIES

The effectiveness of BRIVIACT in partial-onset seizures with or without secondary generalization was established in 3 fixed-dose, randomized, double-blind, placebo-controlled, multicenter studies (Studies 1, 2, and 3), which included 1550 patients. Patients enrolled had partial-onset seizures that were not adequately controlled with 1 to 2 concomitant antiepileptic drugs (AEDs). In each of these studies, 72% to 86% of patients were taking 2 or more concomitant AEDs with or without vagal nerve stimulation. The median baseline seizure frequency across the 3 studies was 9 seizures per 28 days. Patients had a mean duration of epilepsy of approximately 23 years.

All trials had an 8-week baseline period, during which patients were required to have at least 8 partial-onset seizures. The baseline period was followed by a 12-week treatment period. There was no titration period in these studies. Study 1 compared doses of BRIVIACT 50 mg/day and 100 mg/day with placebo. Study 2 compared a dose of BRIVIACT 50 mg/day with placebo. Study 3 compared doses of BRIVIACT 100 mg/day and 200 mg/day with placebo. BRIVIACT was administered in equally divided twice daily doses. Upon termination of BRIVIACT treatment, patients were down-titrated over a 1-, 2-, and 4-week duration for patients receiving 25, 50, and 100 mg twice daily BRIVIACT, respectively.

The primary efficacy outcome in Study 1 and Study 2 was the percent reduction in 7-day partial-onset seizure frequency over placebo, while the primary outcome for Study 3 was the percent reduction in 28-day partial-onset seizure frequency over placebo. The criteria for statistical significance for all 3 studies was p<0.05. Table 6 presents the primary efficacy outcome of the percent change in seizure frequency over placebo, based upon each study's protocol-defined 7- and 28-day seizure frequency efficacy outcome.

Table 6: Percent Reduction in Partial-Onset Seizure Frequency over Placebo (Studies 1, 2, and 3)
 | Percent Reduction Over Placebo (%)
STUDY 1 [Based upon 7-day seizure frequency]
Placebo (n=100) | -------
50 mg/day (n=99) | 9.5
100 mg/day (n=100) | 17.0
STUDY 2
Placebo (n=96) | -------
50 mg/day (n=101) | 16.9 [Statistically significant based on testing procedure with alpha = 0.05]
STUDY 3 [Based upon 28-day seizure frequency]
Placebo (n=259) | ------
100 mg/day (n=252) | 25.2
200 mg/day (n= 249) | 25.7

Figure 1 presents the percentage of patients by category of reduction from baseline in partial-onset seizure frequency per 28 days for all pooled patients in the 3 pivotal studies. Patients in whom the seizure frequency increased are shown at left as "worse." Patients with an improvement in percent reduction from baseline partial-onset seizure frequency are shown in the 4 right-most categories.

Figure 1: Proportion of Patients by Category of Seizure Response for BRIVIACT and Placebo Across all Three Double-Blind Trials

Treatment with Levetiracetam

In Studies 1 and 2, which evaluated BRIVIACT dosages of 50 mg and 100 mg daily, approximately 20% of the patients were on concomitant levetiracetam. Although the numbers of patients were limited, BRIVIACT provided no added benefit when it was added to levetiracetam.

Although patients on concomitant levetiracetam were excluded from Study 3, which evaluated 100 and 200 mg daily, approximately 54% of patients in this study had prior exposure to levetiracetam.

16 HOW SUPPLIED/STORAGE AND HANDLING

16.1 How Supplied

BRIVIACT Tablets

- 10 mg are white to off-white, round, film-coated, and debossed with "u10" on one side. They are supplied as follows:

 | Bottles of 60 tablets | NDC 50474-370-66

- 25 mg are grey, oval, film-coated, and debossed with "u25" on one side. They are supplied as follows:

 | Bottles of 60 tablets | NDC 50474-470-66
 | Unit dose cartons of 100 tablets | NDC 50474-470-09

- 50 mg are yellow, oval, film-coated, and debossed with "u50" on one side. They are supplied as follows:

 | Bottles of 60 tablets | NDC 50474-570-66
 | Unit dose cartons of 100 tablets | NDC 50474-570-09

- 75 mg are purple, oval, film-coated, and debossed with "u75" on one side. They are supplied as follows:

 | Bottles of 60 tablets | NDC 50474-670-66

- 100 mg are green-grey, oval, film-coated, and debossed with "u100" on one side. They are supplied as follows:

 | Bottles of 60 tablets | NDC 50474-770-66
 | Unit dose cartons of 100 tablets | NDC 50474-770-09

BRIVIACT Oral Solution

- 10 mg/mL is a slightly viscous, clear, colorless to yellowish, raspberry-flavored liquid. It is supplied in amber glass bottles:

 | 300 mL bottles | NDC 50474-870-15

BRIVIACT Injection

- 50 mg/5 mL is a clear, colorless, sterile solution supplied in colorless single-dose glass vials.

 | Carton of 10 vials | NDC 50474-970-75

16.2 Storage and Handling

Store at 25°C (77°F); excursions permitted between 15°C to 30°C (59°F to 86°F). See USP Controlled Room Temperature.

Do not freeze BRIVIACT injection or oral solution.

Discard any unused BRIVIACT oral solution remaining after 5 months of first opening the bottle.

BRIVIACT injection vials are single-dose only [see Dosage and Administration (2.3)] .

17 PATIENT COUNSELING INFORMATION

Advise the patient to read the FDA-approved patient labeling (Medication Guide). The Medication Guide accompanies the product and can also be accessed on www.briviact.com or by calling 1-844-599-2273.

Suicidal Behavior and Ideation

Counsel patients, their caregivers, and/or families that antiepileptic drugs, including BRIVIACT, may increase the risk of suicidal thoughts and behavior, and advise patients to be alert for the emergence or worsening of symptoms of depression; unusual changes in mood or behavior; or suicidal thoughts, behavior, or thoughts about self-harm. Advise patients, their caregivers, and/or families to report behaviors of concern immediately to a healthcare provider [see Warnings and Precautions (5.1)] .

Neurological Adverse Reactions

Counsel patients that BRIVIACT causes somnolence, fatigue, dizziness, and gait disturbance. These adverse reactions, if observed, are more likely to occur early in treatment but can occur at any time. Advise patients not to drive or operate machinery until they have gained sufficient experience on BRIVIACT to gauge whether it adversely affects their ability to drive or operate machinery [see Warnings and Precautions (5.2)] .

Psychiatric Adverse Reactions

Advise patients that BRIVIACT causes changes in behavior (e.g., aggression, agitation, anger, anxiety, and irritability) and psychotic symptoms. Instruct patients to report these symptoms immediately to their healthcare provider [see Warnings and Precautions (5.3)] .

Hypersensitivity: Bronchospasm and Angioedema

Advise patients that symptoms of hypersensitivity including bronchospasm and angioedema can occur with BRIVIACT. Instruct them to seek immediate medical care should they experience signs and symptoms of hypersensitivity [see Warnings and Precautions (5.4)] .

Serious Dermatologic Reactions

Advise patients of the early signs and symptoms of serious dermatologic adverse reactions and to report any occurrence immediately to a healthcare provider [see Warnings and Precautions (5.5)].

Withdrawal of Antiepileptic Drugs

Advise patients not to discontinue use of BRIVIACT without consulting with their healthcare provider. BRIVIACT should normally be gradually withdrawn to reduce the potential for increased seizure frequency and status epilepticus [see Warnings and Precautions (5.6)] .

Pregnancy

Advise patients to notify their healthcare provider if they become pregnant or intend to become pregnant during BRIVIACT therapy. Encourage patients to enroll in the North American Antiepileptic Drug Pregnancy Registry if they become pregnant. This registry is collecting information about the safety of antiepileptic drugs during pregnancy [see Use in Specific Populations (8.1)] .

Lactation

Counsel patients that brivaracetam, the active ingredient in BRIVIACT, is present in breast milk. Instruct patients to discuss with their healthcare provider if they are breastfeeding or intend to breastfeed [see Use in Specific Populations (8.2)] .

Dosing Instructions

Counsel patients that BRIVIACT may be taken with or without food. Instruct patients that BRIVIACT tablets should be swallowed whole with liquid and not chewed or crushed [see Dosage and Administration (2.2)].

Advise patients that the dosage of BRIVIACT oral solution should be measured using a calibrated measuring device and not a household teaspoon. Instruct patients to discard any unused BRIVIACT oral solution after 5 months of first opening the bottle [see Dosage and Administration (2.2)].

BRIVIACT Tablets, BRIVIACT Oral Solution, and BRIVIACT Injection manufactured for
UCB, Inc.
Smyrna, GA 30080

BRIVIACT®is a registered trademark of the UCB Group of Companies.
©2025, UCB, Inc., Smyrna, GA 30080
All rights reserved.

MEDICATION GUIDE
BRIVIACT®(briv ee akt) CV
(brivaracetam)
tablets, oral solution, and injection for intravenous use

What is the most important information I should know about BRIVIACT?
BRIVIACT is a federally controlled substance (CV) because it can be abused or lead to dependence. Keep BRIVIACT in a safe place to prevent misuse and abuse. Selling or giving away BRIVIACT may harm others and is against the law.
Like other antiepileptic drugs, BRIVIACT may cause suicidal thoughts or actions in a very small number of people, about 1 in 500 people taking it.
Call a healthcare provider right away if you have any of these symptoms, especially if they are new, worse, or worry you:

- thoughts about suicide or dying
- new or worse depression
- feeling agitated or restless
- trouble sleeping (insomnia)
- acting aggressive, feeling angry, or being violent
- an extreme increase in activity and talking (mania)

- attempts to commit suicide
- new or worse anxiety
- panic attacks
- new or worse irritability
- acting on dangerous impulses
- other unusual changes in behavior or mood

Suicidal thoughts or actions can be caused by things other than medicines. If you have suicidal thoughts or actions, your healthcare provider may check for other causes.

How can I watch for early symptoms of suicidal thoughts and actions?

- Pay attention to any changes, especially sudden changes, in mood, behaviors, thoughts, or feelings.
- Keep all follow-up visits with your healthcare provider as scheduled.

Call your healthcare provider between visits as needed, especially if you are worried about symptoms.

Do not stop BRIVIACT without first talking to a healthcare provider.

- Stopping BRIVIACT suddenly can cause serious problems.
- Stopping a seizure medicine suddenly can cause seizures that will not stop (status epilepticus).

What is BRIVIACT?
BRIVIACT is a prescription medicine used to treat partial-onset seizures in people 1 month of age and older.
It is not known if BRIVIACT is safe and effective in children younger than 1 month of age.

Who should not take BRIVIACT?
Do not take BRIVIACT if you are allergic to brivaracetam or any of the ingredients in BRIVIACT. See the end of this Medication Guide for a complete list of ingredients in BRIVIACT.

What should I tell my healthcare provider before starting BRIVIACT?
Before taking BRIVIACT, tell your healthcare provider about all of your medical conditions, including if you :

- have or had depression, mood problems, or suicidal thoughts or behavior.
- have liver problems.
- have abused or been dependent on prescription medicines, street drugs, or alcohol.
- are pregnant or plan to become pregnant. It is not known if BRIVIACT will harm your unborn baby. Tell your healthcare provider right away if you become pregnant while taking BRIVIACT. You and your healthcare provider will have to decide if you should take BRIVIACT while you are pregnant. If you become pregnant while taking BRIVIACT, talk to your healthcare provider about registering with the North American Antiepileptic Drug Pregnancy Registry. You can enroll in this registry by calling 1-888-233-2334. The purpose of this registry is to collect information about the safety of BRIVIACT and other antiepileptic medicines during pregnancy.
- are breastfeeding or plan to breastfeed. BRIVIACT passes into your breast milk. Talk to your healthcare provider about the best way to feed your baby if you take BRIVIACT.

Tell your healthcare provider about all the medicines you take,including prescription and over-the-counter medicines, vitamins, and herbal supplements. BRIVIACT may affect the way other medicines work, and other medicines may affect how BRIVIACT works. Do not start a new medicine without first talking with your healthcare provider. Know the medicines you take. Keep a list of them to show your healthcare provider and pharmacist each time you get a new medicine.

How should I take BRIVIACT?

- Take BRIVIACT exactly as your healthcare provider tells you.
- Your healthcare provider will tell you how much BRIVIACT to take and when to take it.
- Your healthcare provider may change your dose if needed. Do not change your dose without talking to your healthcare provider.
- Take BRIVIACT with or without food.
- Swallow BRIVIACT tablets whole with a liquid. Do not chew or crush BRIVIACT tablets before swallowing.
- If your healthcare provider has prescribed BRIVIACT oral solution, be sure to ask your pharmacist for a medicine dropper or medicine cup to help you measure the correct amount of BRIVIACT oral solution. Do not use a household teaspoon or tablespoon. Ask your pharmacist for instructions on how to use the measuring device the right way.
- BRIVIACT injection can be given to you by intravenous (IV) infusion into your vein, as prescribed by your healthcare provider.
- If you take too much BRIVIACT, call your Poison Control Center or go to the nearest emergency room right away.

What should I avoid while taking BRIVIACT?
Do not drive or operate machinery until you know how BRIVIACT affects you. BRIVIACT may cause drowsiness, tiredness, dizziness, and problems with your balance and coordination.

What are the possible side effects of BRIVIACT?
BRIVIACT may cause serious side effects, including:

- See " What is the most important information I should know about BRIVIACT?"
- Nervous system problems.Drowsiness, tiredness, and dizziness are common with BRIVIACT, but can be severe. See " What should I avoid while taking BRIVIACT?" BRIVIACT can also cause problems with balance and coordination.
- Mental (psychiatric) symptoms.BRIVIACT can cause mood and behavior changes such as aggression, agitation, anger, anxiety, apathy, mood swings, depression, hostility, and irritability. Irritability and anxiety are common with BRIVIACT, and can be severe. People who take BRIVIACT can also get psychotic symptoms such as hallucinations (seeing or hearing things that are really not there), delusions (false or strange thoughts or beliefs), and unusual behavior.
- Serious allergic reactions.Stop taking BRIVIACT and call your healthcare provider right away if you have any of these signs of a serious allergic reaction:
  - swelling of your face, mouth, lips, gums, tongue, throat, or neck
  - trouble breathing
- Serious skin rashes.BRIVIACT may cause a severe rash with blisters and peeling skin. This may occur around the mouth, nose, eyes, and genitals or over much of the body. A mild rash may become a serious reaction and may cause death. Call your healthcare provider right away if you have a rash, skin blisters, sores in the mouth, or hives. Do not stop taking BRIVIACT without first talking to your healthcare provider.

The most common side effects of BRIVIACT in adults include:

- sleepiness
- dizziness

- feeling tired
- nausea and vomiting

Side effects of BRIVIACT in children 1 month to less than 16 years of age are similar to those seen in adults.
These are not all the possible side effects of BRIVIACT. For more information, ask your healthcare provider or pharmacist. Tell your healthcare provider about any side effect that bothers you or that does not go away. Call your doctor for medical advice about side effects. You may report side effects to FDA at 1-800-FDA-1088.

How should I store BRIVIACT?

- Store BRIVIACT at room temperature between 59°F to 86°F (15°C to 30°C).
- Do not freeze BRIVIACT oral solution.
- Safely throw away any opened bottle of BRIVIACT oral solution after 5 months of first opening the bottle, even if there is medicine left in the bottle.

Keep BRIVIACT and all medicines out of the reach of children.

General information about the safe and effective use of BRIVIACT.
Medicines are sometimes prescribed for purposes other than those listed in a Medication Guide. Do not use BRIVIACT for a condition for which it was not prescribed. Do not give BRIVIACT to other people, even if they have the same symptoms that you have. It may harm them.
This Medication Guide summarizes the most important information about BRIVIACT. If you would like more information, talk with your healthcare provider. You can ask your pharmacist or healthcare provider for information about BRIVIACT that is written for health professionals .

What are the ingredients in BRIVIACT?
Active ingredient: brivaracetam
Tablet inactive ingredients:croscarmellose sodium, lactose monohydrate, betadex (β-cyclodextrin), anhydrous lactose, and magnesium stearate. The tablet film coating contains the inactive ingredients listed below:

- 10 mg tablets:polyvinyl alcohol, talc, polyethylene glycol 3350, titanium dioxide
- 25 mg and 100 mg tablets:polyvinyl alcohol, talc, polyethylene glycol 3350, titanium dioxide, yellow iron oxide, black iron oxide
- 50 mg tablets:polyvinyl alcohol, talc, polyethylene glycol 3350, titanium dioxide, yellow iron oxide, red iron oxide
- 75 mg tablets:polyvinyl alcohol, talc, polyethylene glycol 3350, titanium dioxide, yellow iron oxide, red iron oxide, black iron oxide

Oral solution inactive ingredients:sodium citrate, anhydrous citric acid, methylparaben, sodium carboxymethylcellulose, sucralose, sorbitol solution, glycerin, raspberry flavor, and purified water.
Injection inactive ingredients: sodium acetate, trihydrate (1.64 mg/mL), glacial acetic acid (for pH adjustment to 5.5), sodium chloride (9.00 mg/mL), and water for injection.

Manufactured for UCB, Inc., Smyrna, GA 30080.
BRIVIACT®is a registered trademark of the UCB Group of Companies. ©2025, UCB, Inc., Smyrna, GA 30080. All rights reserved.
For more information, go to www.BRIVIACT.com or call 1-844-599-2273.

This Medication Guide has been approved by the U.S. Food and Drug Administration

Revised: 8/2025

PRINCIPAL DISPLAY PANEL - 10 mg Tablet Bottle Carton

NDC 50474-370-66
Rx only

BRIVIACT®
(brivaracetam)
tablets
CV

10 mg

ATTENTION PHARMACIST:
Dispense accompanying
medication guide to each patient.

60 tablets

PRINCIPAL DISPLAY PANEL - 25 mg Tablet Bottle Carton

NDC 50474-470-66
Rx only

BRIVIACT®
(brivaracetam)
tablets
CV

25 mg

ATTENTION PHARMACIST:
Dispense accompanying
medication guide to each patient.

60 tablets

PRINCIPAL DISPLAY PANEL - 50 mg Tablet Bottle Carton

NDC 50474-570-66
Rx only

BRIVIACT®
(brivaracetam)
tablets
CV

50 mg

ATTENTION PHARMACIST:
Dispense accompanying
medication guide to each patient.

60 tablets

PRINCIPAL DISPLAY PANEL - 75 mg Tablet Bottle Carton

NDC 50474-670-66
Rx only

BRIVIACT®
(brivaracetam)
tablets
CV

75 mg

ATTENTION PHARMACIST:
Dispense accompanying
medication guide to each patient.

60 tablets

PRINCIPAL DISPLAY PANEL - 100 mg Tablet Bottle Carton

NDC 50474-770-66
Rx only

BRIVIACT®
(brivaracetam)
tablets
CV

100 mg

ATTENTION PHARMACIST:
Dispense accompanying
medication guide to each patient.

60 tablets

PRINCIPAL DISPLAY PANEL - 300 mL Bottle Carton

NDC 50474-870-15
Rx only

BRIVIACT®
(brivaracetam)
oral solution
CV

10 mg/mL

ATTENTION PHARMACIST:
Dispense accompanying
medication guide to
each patient

300 mL

PRINCIPAL DISPLAY PANEL - 10 Vial Carton

NDC 50474-970-75
Rx only

BRIVIACT®
(brivaracetam) injection CV

50 mg/5 mL
(10 mg/mL)

For Intravenous Use Only

10 vials